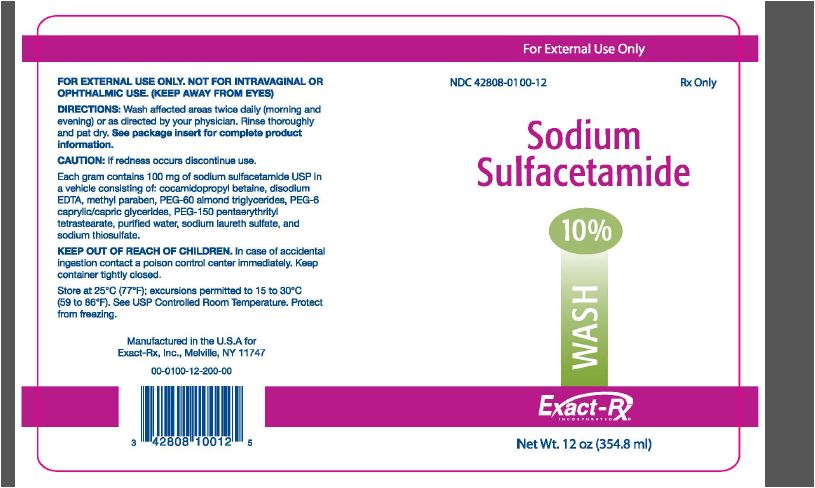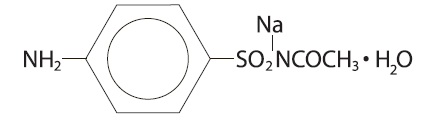 DRUG LABEL: SODIUM SULFACETAMIDE
NDC: 42808-100 | Form: LIQUID
Manufacturer: Exact-Rx, Inc.
Category: prescription | Type: HUMAN PRESCRIPTION DRUG LABEL
Date: 20110801

ACTIVE INGREDIENTS: SULFACETAMIDE SODIUM 100 mg/1 mL
INACTIVE INGREDIENTS: COCAMIDOPROPYL BETAINE; EDETATE DISODIUM; METHYLPARABEN; PEG-60 ALMOND GLYCERIDES; CAPRYLIC/CAPRIC MONO/DIGLYCERIDES; WATER; SODIUM LAURETH SULFATE; SODIUM THIOSULFATE

SODIUM SULFACETAMIDE 10% WASH
(sodium sulfacetamide 10%)
Rx Only

FOR EXTERNAL USE ONLY.
NOT FOR OPHTHALMIC USE.

DESCRIPTION

DESCRIPTION: Each gram contains 100 mg of sodium sulfacetamide USP in a vehicle consisting of: cocamidopropyl betaine, disodium EDTA, methyl paraben, PEG-60 almond triglyceride, PEG-6 caprylic/capric glycerides, PEG-150 pentaerythrityl tetrastearate, purified water, sodium laureth sulfate, and sodium thiosulfate.

Chemically, it is Acetamide N-[4-aminophenyl)sulfonyl]-, monosodium salt, monohydrate, with the following structural formula:

Sodium sulfacetamide is an odorless, white, crystalline powder with a bitter taste. It is freely soluble in water, sparingly soluble in alcohol, while practically insoluble in benzene, in chloroform, and in ether.

CLINICAL PHARMACOLOGY

CLINICAL PHARMACOLOGY: Sodium sulfacetamide exerts a bacteriostatic effect against sulfonamide sensitive Gram-positive and Gram-negative microorganisms commonly isolated from secondary cutaneous pyogenic infections. It acts by restricting the synthesis of folic acid required by bacteria for growth, by its competition with para-aminobenzoic acid. There are no clinical data available on the degree and rate of systemic competition with para-aminobenzoic acid absorption of Sodium Sulfacetamide 10% Wash when applied to the skin or scalp. However, significant absorption of sodium sulfacetamide through the skin has been reported. The following in vitro data are available but their clinical significance is unknown. Organisms which show susceptibility to sodium sulfacetamide are: Streptococci, Staphylococci, E. coli, Klebsiella pneumoniae, Pseudomonas pyocyanea, Salmonella species, Proteus vulgaris, Nocardia and Actinomyces.

INDICATIONS AND USAGE: Sodium Sulfacetamide 10% Wash is intended for topical application in the following scaling dematoses: seborrheic dermatitis and sebonthea sicca (dandruff). It also is indicated for the treatment of secondary bacterial infections of the skin due to organisms susceptible to sulfonamides.

CONTRAINDICATIONS

CONTRAINDICATIONS: Sodium Sulfacetamide 10% Wash is contraindicated in persons with known or suspected hypersensitivity to sulfonamides or to any of the ingredients of the product.

WARNINGS

WARNINGS: Sulfonamides are known to cause Stevens-Johnson syndrome in hypersensitive individuals. Stevens-Johnson syndrome also has been reported following the use of sodium sulfacetamide topically.

Cases of drug-induced systemic lupus erythematosus from topical sulfacetamide also have been reported. In one of these cases, there was a fatal outcome. Keep out of the reach of children.

PRECAUTIONS

PRECAUTIONS: For external use only. Not for ophthalmic use. General: Nonsusceptible organisms, including fungi, may proliferate with the use of this preparation. Hypersensitivity reactions may recur when a sulfonamide is readministered, irrespective of the route of administration, and cross hypersensitivity between different sulfonamides may occur. If Sodium Sulfacetamide 10% Wash produces signs of hypersensitivity or other untoward reactions, discontinue use of the preparation. Systemic absorption of topical sulfonamides is greater following application to large, infected, abraded, denuded, or severely burned areas. Under these circumstances, potentially any of the adverse effects produced by the systemic administration of these agents could occur and appropriate observations and laboratory determinations should be performed.

PATIENT COUNSELING INFORMATION

Information For Patients: Patients should discontinue Sodium Sulfacetamide 10% Wash if the condition becomes worse, or if a rash develops in the area being treated or elsewhere. Sodium Sulfacetamide 10% Wash also should be discontinued promptly and the physician notified if any arthritis, fever, or sores in the mouth develop.

DRUG INTERACTIONS

Drug Interactions: Sodium Sulfacetamide 10% Wash is incompatible with silver preparations.

Pharmacology: Sodium Sulfacetamide 10% Wash has a bacterlostatic effect against Gram-positive and Gram-negative microorganisms commonly isolated from secondary cutaneous pyogenic infections.

CARCINOGENESIS AND MUTAGENESIS AND IMPAIRMENT OF FERTILITY

Carcinogenesis, Mutagenesis, Impairment of Fertility: Long-term animal studies for carcinogenic potential have not been performed on Sodium Sulfacetamide 10% Wash to date. Studies on reproduction and fertility also have not been performed. Chromosomal nondisjunction in the yeast, Saccharomyces cerevisiae, following application of sulfacetamide sodium has been reported. The significance of this finding to the topical use of sulfacetamide sodium in the human is unknown.

PREGNANCY

Pregnancy Category C: Animal reproduction studies have not been conducted with Sodium Sulfacetamide 10% Wash. It also is not known whether Sodium Sulfacetamide 10% Wash can cause fetal harm when administered to a pregnant woman or can affect reproduction capacity. Sodium Sulfacetamide 10% Wash should be used by a pregnant woman only if clearly needed or when potential benefits outweigh potential hazards to the fetus.

NURSING MOTHERS

Nursing Mothers: It is not known whether this drug is excreted in human milk. Because many drugs are excreted in human milk, caution should be exercised when Sodium Sulfacetamide 10% Wash is administered to a nursing woman.

PEDIATRIC USE

Pediatric Use: Safety and effectiveness in children under the age of 12 years have not been established.

ADVERSE REACTIONS

ADVERSE REACTIONS: Reports of irritation and hypersensitivity to sodium sulfacetamide are uncommon. The following adverse reactions, reported after administration of sterile ophthalmic sodium sulfacetamide, are noteworthy: instances of Stevens-Johnson syndrome and instances of local hypersensitivity which progressed to a syndrome resembling systemic lupus erythematosus; in one case a fatal outcome was reported (see WARNINGS.) Call your doctor for medical advice about side effects.

OVERDOSAGE

OVERDOSAGE: The oral LD50 of sulfacetamide in mice is 16.5 g/kg. In the event of overdosage, emergency treatment should be started immediately. Manifestations: Overdosage may cause nausea and vomiting. Large oral overdosage may cause hematuria, crystalluiria, and renal shutdown due to the precipitation of sulfa crystals in the renal tubules and the urinary tract. For treatment, contact your local Poison Control Center.

DOSAGE AND ADMINISTRATION: Seborrheic dermatitis including seborrhea sicca - Sodium Sulfacetamide 10% Wash: Wash affected areas twice daily (morning and evening), or as directed by your physician. Avoid contact with eyes or mucous membranes. Wet skin and liberally apply to areas to be cleansed, massage gently into skin working into a full lather, rinse thoroughly/pat dry and repeat after 10-20 seconds. Rinsing with plain water will remove any excess medication. Repeat application as described for eight to ten days. If skin dryness occurs it may be controlled by rinsing cleanser off sooner or using less frequently. Regular shampooing following Sodium Sulfacetamide 10% Wash is not necessary, but the hair should be shampooed at least once a week. As the condition subsides, the interval between applications may be lengthened. Applications once or twice weekly or every other week may prevent recurrence. Should the condition recur after stopping therapy, the application of Sodium Sulfacetamide 10% Wash should be reinitiated as at the beginning of treatment.

Secondary cutaneous bacterial infections - Wet skin and liberally apply to areas to be cleansed, massage gently into skin for 10-20 seconds working into a full lather, rinse thoroughly and pat dry. Rinsing with plain water will remove any excess medication. Repeat application as described for eight to ten days. If skin dryness occurs it may be controlled by rinsing cleanser off sooner or using less often.

HOW SUPPLIED

HOW SUPPLIED: Sodium Sulfacetamide Wash 10% is available in a 6 oz. (177 mL) bottle, NDC 42808-0100-06, and in a 12 oz. (354.8 mL) bottle, NDC 42808-0100-12.

STORAGE AND HANDLING

STORAGE: Store at 25°C (77°F); excursions permitted to 15°-30°C (59°-86°F). See USP Controlled Room Temperature. Protect from freezing.

Note: Store upright. Protect from freezing and excessive heat. The wash may tend to darken slightly on storage. Slight discoloration does not impair the efficacy or safety of the product.

Occasionally, a slight yellowish discoloration may occur when an excessive amount of the product is used and comes in contact with white fabrics. This discoloration is readily removed by ordinary laundering without bleaches.

Manufactured in the U.S.A. for Exact-Rx, Inc., Melville, NY 11747

00-0100-99-205-00

Iss:5/11

PACKAGE LABEL - 12 oz (354.8 mL)

For External Use Only

NDC 42808-0100-06 Rx Only

Sodium
Sulfacetamide

10%

WASH

Exact-Rx.
INCORPORATED

Net Wt. 12 oz (354.8 ml)